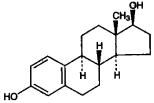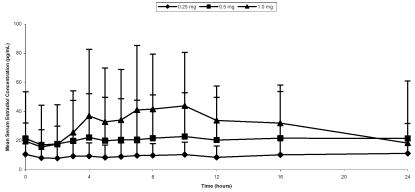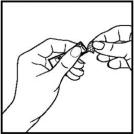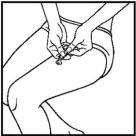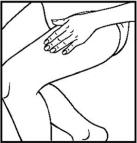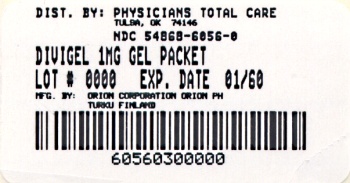 DRUG LABEL: Divigel
NDC: 54868-6056 | Form: GEL
Manufacturer: Physicians Total Care, Inc.
Category: prescription | Type: HUMAN PRESCRIPTION DRUG LABEL
Date: 20090831

ACTIVE INGREDIENTS: ESTRADIOL 1.0 mg/1 g
INACTIVE INGREDIENTS: CARBOMER HOMOPOLYMER TYPE C; ALCOHOL; PROPYLENE GLYCOL; WATER; TROLAMINE

Divigel®
(estradiol gel) 0.1%

Rx only

BOXED WARNING

ESTROGENS INCREASE THE RISK OF ENDOMETRIAL CANCER

Close clinical surveillance of all women taking estrogens is important. Adequate diagnostic measures, including endometrial sampling when indicated, should be undertaken to rule out malignancy in all cases of undiagnosed persistent or recurring abnormal vaginal bleeding. There is no evidence that the use of "natural" estrogens results in a different endometrial risk profile than synthetic estrogens at equivalent estrogen doses. (See WARNINGS, Malignant neoplasms, Endometrial cancer.)

CARDIOVASCULAR AND OTHER RISKS

Estrogens with or without progestins should not be used for the prevention of cardiovascular disease or dementia. (See CLINICAL STUDIES and WARNINGS, Cardiovascular disorders and Dementia.)

The estrogen-alone substudy of the Women's Health Initiative (WHI) reported increased risks of stroke and deep vein thrombosis in postmenopausal women (50 to 79 years of age) during 6.8 years and 7.1 years, respectively, of treatment with oral conjugated estrogens (CE 0.625 mg) alone per day, relative to placebo. (See CLINICAL STUDIES and WARNINGS, Cardiovascular disorders.)

The estrogen-plus-progestin substudy of the WHI reported increased risk of myocardial infarction, stroke, invasive breast cancer, pulmonary emboli, and deep vein thrombosis in postmenopausal women (50 to 79 years of age) during 5.6 years of treatment with oral conjugated estrogens (CE 0.625 mg) combined with medroxyprogesterone acetate (MPA 2.5 mg) per day, relative to placebo. (See CLINICAL STUDIES and WARNINGS, Cardiovascular disorders and Malignant neoplasms, Breast cancer.)

The Women's Health Initiative Memory Study (WHIMS), a substudy of the WHI, reported an increased risk of developing probable dementia in postmenopausal women 65 years of age or older during 5.2 years of treatment with CE 0.625 mg alone and during 4 years of treatment with CE 0.625 mg combined with MPA 2.5 mg, relative to placebo. It is unknown whether this finding applies to younger postmenopausal women. (See CLINICAL STUDIES, WARNINGS, Dementia, and PRECAUTIONS, Geriatric Use.)

Other doses of oral conjugated estrogens with medroxyprogesterone acetate, and other combinations and dosage forms of estrogens and progestins were not studied in the WHI clinical trials and, in the absence of comparable data, these risks should be assumed to be similar. Because of these risks, estrogens with or without progestins should be prescribed at the lowest effective doses and for the shortest duration consistent with treatment goals and risks for the individual woman.

DESCRIPTION

Divigel® (estradiol gel) 0.1% is a clear, colorless gel, which is odorless when dry. It is designed to deliver sustained circulating concentrations of estradiol when applied once daily to the skin. The gel is applied to a small area (200 cm^2) of the thigh in a thin, quick-drying layer. Divigel® is available in three doses of 0.25, 0.5, and 1.0 g for topical application (corresponding to 0.25, 0.5, and 1.0 mg estradiol, respectively).

The active component of the topical gel is estradiol.

Estradiol is a white crystalline powder, chemically described as estra-1,3,5(10)-triene-3,17β-diol. It has an empirical formula of C18H24O2 and molecular weight of 272.39. The structural formula is:

The remaining components of the gel (carbomer, ethanol, propylene glycol, purified water, and triethanolamine) are pharmacologically inactive.

CLINICAL PHARMACOLOGY

Divigel® provides estrogen therapy by delivering estradiol, the major estrogenic hormone secreted by the human ovary, to the systemic circulation following topical application.

Endogenous estrogens are largely responsible for the development and maintenance of the female reproductive system and secondary sexual characteristics. Although circulating estrogens exist in a dynamic equilibrium of metabolic interconversions, estradiol is the principal intracellular human estrogen and is substantially more potent than its metabolites, estrone and estriol, at the receptor level.

The primary source of estrogen in normally cycling adult women is the ovarian follicle, which secretes 70 to 500 mcg of estradiol daily, depending on the phase of the menstrual cycle. After menopause, most endogenous estrogen is produced by conversion of androstenedione, secreted by the adrenal cortex, to estrone by peripheral tissues. Thus, estrone and the sulfate conjugated form, estrone sulfate, are the most abundant circulating estrogens in postmenopausal women.

Estrogens act through binding to nuclear receptors in estrogen-responsive tissues. To date, two estrogen receptors have been identified. These vary in proportion from tissue to tissue.

Circulating estrogens modulate the pituitary secretion of the gonadotropins, luteinizing hormone (LH) and follicle-stimulating hormone (FSH), through a negative feedback mechanism. Estrogens act to reduce the elevated levels of these hormones seen in postmenopausal women.

Pharmacokinetics

A. Absorption

Estradiol diffuses across intact skin and into the systemic circulation by a passive absorption process, with diffusion across the stratum corneum being the rate-limiting factor.

In a 14-day, Phase 1, multiple-dose study, Divigel® demonstrated linear and approximately dose-proportional estradiol pharmacokinetics at steady state for both AUC0-24 and Cmax following once daily dosing to the skin of either the right or left upper thigh (Table 1).

Table 1: Mean (%CV) Pharmacokinetic Parameters for Estradiol (uncorrected for baseline) on Day 14 Following Multiple Daily Doses of Divigel® 0.1%
Parameter (units) | Divigel® 0.25 g | Divigel® 0.5 g | Divigel® 1.0 g
AUC0-24 (pg•h/mL) | 236 (94) | 504 (149) | 732 (81)
Cmax (pg/mL) | 14.7 (84) | 28.4 (139) | 51.5 (86)
Cavg (pg/mL) | 9.8 (92) | 21 (148) | 30.5 (81)
tmax* (h) | 16 (0, 72) | 10 (0, 72) | 8 (0, 48)
E2:E1 ratio | 0.42 | 0.65 | 0.65
*Median (Min, Max).

Steady-state serum concentration of estradiol are achieved by day 12 following daily application of Divigel® to the skin of the upper thigh. The mean (SD) serum estradiol levels following once daily dosing at day 14 are shown in Figure 1.

Figure 1: Mean (SD) Serum Estradiol Concentrations (Values Uncorrected for Baseline) on Day 14 Following Multiple Daily Doses of Divigel 0.1%

The effect of sunscreens and other topical lotions on the systemic exposure of Divigel® has not been evaluated. Studies conducted using topical estrogen gel approved products have shown that sunscreens have the potential for changing the systemic exposure of topically applied estrogen gels.

B. Distribution

The distribution of exogenous estrogens is similar to that of endogenous estrogens. Estrogens are widely distributed in the body and are generally found in higher concentrations in the sex hormone target organs. Estrogens circulate in the blood largely bound to sex hormone binding globulin (SHBG) and albumin.

C. Metabolism

Circulating estrogens exist in a dynamic equilibrium of metabolic interconversions. These transformations take place mainly in the liver. Estradiol is converted reversibly to estrone, and both can be converted to estriol, which is the major urinary metabolite. Estrogens also undergo enterohepatic recirculation via sulfate and glucuronide conjugation in the liver, biliary secretion of conjugates into the intestine, and hydrolysis in the intestine followed by reabsorption. In postmenopausal women, a significant proportion of the circulating estrogens exist as sulfate conjugates, especially estrone sulfate, which serves as a circulating reservoir for the formation of more active estrogens.

Estradiol from Divigel® avoids first pass metabolism and provides estradiol/estrone ratios at steady state in the range of 0.42 to 0.65.

D. Excretion

Estradiol, estrone, and estriol are excreted in the urine along with glucuronide and sulfate conjugates. The apparent terminal half-life for estradiol was about 10 hours following administration of Divigel®.

E. Special Populations

Divigel® has been studied only in postmenopausal women. No pharmacokinetic studies were conducted in special populations, including patients with renal or hepatic impairment.

F. Drug Interactions

In vitro and in vivo studies have shown that estrogens are metabolized partially by cytochrome P450 3A4 (CYP3A4). Therefore, inducers or inhibitors of CYP3A4 may affect estrogen drug metabolism. Inducers of CYP3A4, such as St. John's Wort preparations (Hypericum perforatum), phenobarbital, carbamazepine, and rifampin, may reduce plasma concentrations of estrogens, possibly resulting in a decrease in therapeutic effects and/or changes in the uterine bleeding profile. Inhibitors of CYP3A4, such as erythromycin, clarithromycin, ketoconazole, itraconazole, ritonavir, and grapefruit juice, may increase plasma concentrations of estrogens and result in side effects.

G. Potential for Estradiol Transfer and Effects of Washing

As with most topical products, there is a potential for estradiol transfer following physical contact with Divigel® application sites. The effect of estradiol transfer was evaluated in healthy postmenopausal women who topically applied 1.0 g of Divigel® (single dose) on one thigh. One and 8 hours after gel application, they engaged in direct thigh- to- arm contact with a partner for 15 minutes. While some elevation of estradiol levels over baseline was seen in the male subjects, the degree of transferability in this study was inconclusive.

The effect of application site washing on skin surface levels and serum concentrations of estradiol was determined in 16 healthy postmenopausal women after application of 1.0 g of Divigel® to a 200 cm^2 area on the thigh. Washing the application site with soap and water 1 hour after application removed all detectable amounts of estradiol from the surface of the skin, and resulted in a 30-38% decrease in the mean total 24-hour exposure to estradiol.

Clinical Studies

Effects on Vasomotor Symptoms

A randomized, double-blind, placebo-controlled trial evaluated the efficacy of 12-week treatment with three different daily doses of Divigel® for vasomotor symptoms in 495 postmenopausal women (86.5% White; 10.1% Black) between 34 and 89 years of age (mean age 54.6) who had at least 50 moderate to severe hot flushes per week at baseline (2 week period prior to treatment). Subjects applied placebo, Divigel® 0.25 g (0.25 mg estradiol), Divigel® 0.5 g (0.5 mg estradiol) or Divigel® 1.0 g (1.0 mg estradiol) once daily to the thigh. Reductions in both the median daily frequency and the median daily severity of moderate to severe hot flushes were statistically significant for the 0.5 g/day and the 1.0 g/day Divigel® doses when compared to placebo at week 4. Statistically significant reductions in both the median daily frequency and the median daily severity of moderate to severe hot flushes for the Divigel® 0.25 g/day dose when compared to placebo were delayed to week 7. There were statistically significant reductions in median daily frequency and severity of hot flushes for all three Divigel® doses (0.25 g/day, 0.5 g/day and 1.0 g/day) compared to placebo at week 12. See Table 2 for results.

Table 2: Summary of Change From Baseline in the Median Daily Frequency and Severity of Hot Flushes during Divigel® Treatment (ITT Population)
 |  | Divigel® |  |  | Placebo
Evaluation |  | 0.25 g/day N=121 | 0.5 g/day N=119 | 1.0 g/day N=124 | N=124
Frequency of Daily Hot Flushes
Baseline Median |  | 9.72 | 9.24 | 9.64 | 9.32
Median Change: Week 4 |  | -5.00 | -5.73 | -7.20 | -3.63
 | p-value† | 0.132 | 0.011 | <0.001
Median Change: Week 7 |  | -6.62 | -7.14 | -7.71 | -4.37
 | p-value† | <0.001 | <0.001 | <0.001
Median Change: Week 12 |  | -6.88 | -7.29 | -8.35 | -4.48
 | p-value† | <0.001 | <0.001 | <0.001
Severity of Daily Hot Flushes
Baseline Median |  | 2.52 | 2.51 | 2.52 | 2.54
Median Change: Week 4 |  | -0.07 | -0.18 | -0.47 | -0.04
 | p-value† | 0.283 | <0.001 | <0.001
Median Change: Week 7 |  | -0.24 | -0.46 | -1.06 | -0.06
 | p-value† | <0.001 | <0.001 | <0.001
Median Change: Week 12 |  | -0.33 | -0.56 | -1.69 | -0.13
 | p-value† | 0.021 | 0.002 | <0.001
†p-values from the van Elteren's test stratified by pooled center; comparison in median change was significant if p<0.05

Women's Health Initiative Studies

The Women's Health Initiative (WHI) enrolled a total of 27,000 predominantly healthy postmenopausal women in two substudies to assess the risks and benefits of either the use of oral conjugated estrogens (CE 0.625 mg) alone per day or in combination with medroxyprogesterone acetate (CE 0.625 mg/MPA 2.5 mg) per day compared to placebo in the prevention of certain chronic diseases. The primary endpoint was the incidence of coronary heart disease (CHD) (nonfatal myocardial infarction (MI), silent MI and CHD death), with invasive breast cancer as the primary adverse outcome studied. A "global index" included the earliest occurrence of CHD, invasive breast cancer, stroke, pulmonary embolism (PE), endometrial cancer (only in the estrogen-plus-progestin substudy), colorectal cancer, hip fracture, or death due to other cause. The study did not evaluate the effects of CE or CE/MPA on menopausal symptoms.

The estrogen-alone substudy was stopped early because an increased risk of stroke was observed and it was deemed that no further information would be obtained regarding the risks and benefits of estrogen alone in predetermined primary endpoints. Results of the estrogen-alone substudy, which included 10,739 women (average age of 63 years, range 50 to 79; 75.3% White, 15.1% Black, 6.1% Hispanic, 3.6% Other), after an average follow-up of 6.8 years are presented in Table 3.

Table 3: Relative And Absolute Risk Seen In The Estrogen-Alone Substudy Of WHIa
Event | Relative Risk CE vs. Placebo | Placebo n = 5,429 | CE n = 5,310
 | (95% nCIa) | Absolute Risk per 10,000 Women-Years
CHD eventsb | 0.95 (0.79- 1.16) | 56 | 53
Nonfatal MIb | 0.91 (0.73-1.14) | 43 | 40
CHD deathb | 1.01 (0.71- 1.43) | 16 | 16
Strokec | 1.39 (1.10-1.77) | 32 | 44
Deep vein thrombosisb,d | 1.47 (1.06-2.06) | 15 | 23
Pulmonary embolismb | 1.37 (0.90-2.07) | 10 | 14
Invasive breast cancerb | 0.80 (0.62-1.04) | 34 | 28
Colorectal cancerc | 1.08 (0.75-1.55) | 16 | 17
Hip fracturec | 0.61 (0.41-0.91) | 17 | 11
Vertebral fracturesc,d | 0.62 (0.42-0.93) | 17 | 11
Total fracturesc,d | 0.70 (0.63-0.79) | 195 | 139
Death due to other causesc,e | 1.08 (0.88-1.32) | 50 | 53
Overall mortalityc,d | 1.04 (0.88-1.32) | 78 | 81
Global indexc,f | 1.01 (0.91-1.12) | 190 | 192
a Nominal confidence intervals unadjusted for multiple looks and multiple comparisons
b Results are based on centrally adjudicated data for an average follow-up of 7.1 years
c Results are based on an average follow-up of 6.8 years
d Not included in Global Index
e All deaths, except from breast or colorectal cancer, definite/probable CHD, PE or cerebrovascular disease
f A subset of the events was combined in a “global index”, defined as the earliest occurrence of CHD events, invasive breast cancer, stroke, pulmonary embolism, colorectal cancer, hip fracture, or death due to other causes

For those outcomes included in the WHI “global index” that reached statistical significance, the absolute excess risk per 10,000 women-years in the group treated with CE alone was 12 more strokes, while the absolute risk reduction per 10,000 women-years was 6 fewer hip fractures. The absolute excess risk of events included in the “global index” was a nonsignificant 2 events per 10,000 women-years. There was no difference between the groups in terms of all-cause mortality. (See BOXED WARNINGS, WARNINGS, and PRECAUTIONS.)

Final centrally adjudicated results for CHD events and centrally adjudicated results for invasive breast cancer incidence from the estrogen-alone substudy, after an average follow-up of 7.1 years, reported no overall difference for primary CHD events (nonfatal MI, silent MI and CHD death) and invasive breast cancer incidence in women receiving CE alone compared with placebo (see Table 3).

The estrogen-plus-progestin substudy was also stopped early because, according to the predefined stopping rule, after an average follow-up of 5.2 years of treatment, the increased risk of breast cancer and cardiovascular events exceeded the specified benefits included in the "global index.” The absolute excess risk of events included in the “global index” was 19 per 10,000 women-years (RR 1.15, 95% nCI 1.03-1.28).

For those outcomes included in the WHI “global index” that reached statistical significance after 5.6 years of follow-up, the absolute excess risks per 10,000 women years in the group treated with CE/MPA were 6 more CHD events, 7 more strokes, 10 more PEs, and 8 more invasive breast cancers, while the absolute risk reductions per 10,000 women-years were 7 fewer colorectal cancers and 5 fewer hip fractures. (See BOXED WARNINGS, WARNINGS, and PRECAUTIONS.)

Results of the estrogen-plus-progestin substudy, which included 16,608 women (average age of 63 years, range 50 to 79; 83.9% White, 6.8% Black, 5.4% Hispanic, 3.9% Other), are presented in Table 4 below. These results reflect centrally adjudicated data after an average follow-up of 5.6 years.

Table 4: Relative And Absolute Risk Seen in the Estrogen-Plus Progestin Substudy of WHI at an Average of 5.6 Yearsa
Eventc | Relative Risk CE/MPA vs. Placebo | Placebo n = 8102 | CE/MPA n = 8506
 | (95% nCIb) | Absolute Risk per 10,000 women-years
CHD events | 1.24 (1.00-1.54) | 33 | 39
Non-fatal MI | 1.28 (1.00-1.63) | 25 | 31
CHD death | 1.10 (0.70-1.75) | 8 | 8
All strokes | 1.31 (1.02-1.68) | 24 | 31
Ischemic stroke | 1.44 (1.09 -1.90) | 18 | 26
Deep vein thrombosis | 1.95 (1.43 – 2.67) | 13 | 26
Pulmonary embolism | 2.13 (1.45-3.11) | 8 | 18
Invasive breast cancerc | 1.24 (1.01-1.54) | 33 | 41
Invasive colorectal cancer | 0.56 (0.38-0.81) | 16 | 9
Endometrial cancer | 0.81 (0.48-1.36) | 7 | 6
Cervical cancer | 1.44 (0.47-4.42) | 1 | 2
Hip fracture | 0.67 (0.47-0.96) | 16 | 11
Vertebral fractures | 0.65 (0.46-0.92) | 17 | 11
Lower arm/wrist fractures | 0.71 (0.59-0.85) | 62 | 44
Total fractures | 0.76 (0.69-0.83) | 199 | 152
a Results are based on centrally adjudicated data. Mortality data was not part of the adjudicated data; however, data at 5.2 years of follow-up showed no difference between the groups in terms of all-cause mortality (RR 0.98, 95% nCI 0.82-1.18)
b Nominal confidence intervals unadjusted for multiple looks and multiple comparisons.
c Includes metastatic and non-metastatic breast cancer, with the exception of in situ breast cancer

Women's Health Initiative Memory Study

The estrogen-alone Women's Health Initiative Memory Study (WHIMS), a substudy of the WHI, enrolled 2,947 predominantly healthy postmenopausal women 65 years of age and older (45% were aged 65 to 69 years, 36% were 70 to 74 years, and 19% were 75 years of age and older) to evaluate the effects of conjugated estrogens (CE 0.625 mg) on the incidence of probable dementia (primary outcome) compared with placebo.

After an average follow-up of 5.2 years, 28 women in the estrogen-alone group (37 per 10,000 women-years) and 19 in the placebo group (25 per 10,000 women-years) were diagnosed with probable dementia. The relative risk of probable dementia in the estrogen-alone group was 1.49 (95% confidence interval (CI), 0.83-2.66) compared to placebo. It is unknown whether these findings apply to younger postmenopausal women. (See BOXED WARNINGS, WARNINGS, Dementia, and PRECAUTIONS, Geriatric Use.)

The estrogen-plus-progestin WHIMS substudy enrolled 4,532 predominantly healthy postmenopausal women 65 years of age and older (47% were aged 65 to 69 years, 35% were 70 to 74 years, and 18% were 75 years of age and older) to evaluate the effects of conjugated estrogens (CE 0.625 mg) plus medroxyprogesterone acetate (MPA 2.5 mg) daily on the incidence of probable dementia (primary outcome) compared with placebo.

After an average follow-up of 4 years, 40 women in the estrogen-plus-progestin group (45 per 10,000 women-years) and 21 in the placebo group (22 per 10,000 women-years) were diagnosed with probable dementia. The relative risk of probable dementia in the hormone therapy group was 2.05 (95% CI, 1.21-3.48) compared to placebo.

When data from the two populations were pooled as planned in the WHIMS protocol, the reported overall relative risk for probable dementia was 1.76 (95% CI 1.19-2.60). It is unknown whether these findings apply to younger postmenopausal women. (See BOXED WARNING, WARNINGS, Dementia, and PRECAUTIONS, Geriatric Use.)

INDICATIONS AND USAGE

Divigel® (estradiol gel) 0.1% is indicated in the treatment of moderate to severe vasomotor symptoms associated with menopause.

CONTRAINDICATIONS

Estrogen products, including Divigel® (estradiol gel) 0.1%, should not be used in women with any of the following conditions:

1. Undiagnosed abnormal genital bleeding.
2. Known, suspected, or history of cancer of the breast.
3. Known or suspected estrogen-dependent neoplasia.
4. Active deep vein thrombosis, pulmonary embolism, or history of these conditions.
5. Active or recent (e.g., within the past year) arterial thromboembolic disease (e.g., stroke, myocardial infarction).
6. Liver dysfunction or disease.
7. Known hypersensitivity to the ingredients of Divigel®.
8. Known or suspected pregnancy. There is no indication for Divigel® in pregnancy. There appears to be little or no increased risk of birth defects in children born to women who have used estrogens and progestins from oral contraceptives inadvertently during early pregnancy. (See PRECAUTIONS.)

WARNINGS

See BOXED WARNINGS.

1. Cardiovascular Disorders

Estrogen-alone therapy has been associated with an increased risk of stroke and deep vein thrombosis (DVT).

Estrogen-plus progestin therapy has been associated with an increased risk of myocardial infarction as well as stroke, venous thrombosis and pulmonary embolism.

Should any of these occur or be suspected, estrogens should be discontinued immediately.

Risk factors for arterial vascular disease (e.g., hypertension, diabetes mellitus, tobacco use, hypercholesterolemia, and obesity) and/or venous thromboembolism (e.g., personal history or family history of VTE, obesity, and systemic lupus erythematosus) should be managed appropriately.

a. Stroke

In the estrogen-alone substudy of the Women's Health Initiative (WHI), a statistically significant increased risk of stroke was observed in women receiving CE 0.625 mg daily compared to placebo (44 versus 32 per 10,000 women-years). The increase in risk was observed in year 1 and persisted. (See CLINICAL STUDIES.)

In the estrogen-plus-progestin substudy of the WHI study, a statistically significant increased risk of stroke was reported in women receiving CE/MPA 0.625 mg/2.5 mg daily compared to women receiving placebo (31 versus 24 per 10,000 women-years). The increase in risk was demonstrated after the first year and persisted.

b. Coronary heart disease

In the estrogen-alone substudy of WHI, no overall effect on coronary heart disease (CHD) events (defined as non-fatal MI, silent MI, or death, due to CHD) was reported in women receiving estrogen-alone compared to placebo. (See CLINICAL STUDIES.)

In the estrogen-plus-progestin substudy of WHI, no statistically significant increase of CHD events was reported in women receiving CE/MPA compared to women receiving placebo (39 vs. 33 per 10,000 women-years). An increase in relative risk was demonstrated in year one and a trend toward decreasing relative risk was reported in years 2 through 5.

In postmenopausal women with documented heart disease (n=2,763, average age 66.7 years), a controlled clinical trial of secondary prevention of cardiovascular disease (Heart and Estrogen/Progestin Replacement Study (HERS)) treatment with CE/MPA (0.625 mg/2.5 mg per day) demonstrated no cardiovascular benefit. During an average follow-up of 4.1 years, treatment with CE/MPA did not reduce the overall rate of CHD events in postmenopausal women with established coronary heart disease. There were more CHD events in the CE/MPA-treated group than in the placebo group in year 1, but not during the subsequent years. Participation in an open label extension of the original HERS trial (HERS II) was agreed to by 2,321 women. Average follow-up in HERS II was an additional 2.7 years, for a total of 6.8 years overall. Rates of CHD events were comparable among women in the CE/MPA group and the placebo group in HERS, HERS II, and overall.

Large doses of estrogen (5 mg conjugated estrogens per day), comparable to those used to treat cancer of the prostate and breast, have been shown in a large prospective clinical trial in men to increase the risks of non-fatal myocardial infarction, pulmonary embolism, and thrombophlebitis.

c. Venous Thromboembolism

In the estrogen-alone substudy of WHI the risk of VTE (DVT and pulmonary embolism [PE]), was reported to be increased for women taking conjugated estrogens compared to placebo (30 versus 22 per 10,000 women-years), although only the increased risk of DVT reached statistical significance (23 vs. 15 per 10,000 women-years). The increase in VTE risk was demonstrated during the first two years. (See CLINICAL STUDIES.)

In the estrogen-plus-progestin substudy of WHI, a statistically significant two-fold greater rate of VTE, was reported in women receiving CE/MPA compared to women receiving placebo (35 vs. 17 per 10,000 women-years). Statistically significant increases in risk for both DVT (26 vs. 13 per 10,000 women-years) and PE (18 vs. 8 per 10,000 women-years) were also demonstrated. The increase in VTE risk was demonstrated during the first year and persisted. (See CLINICAL STUDIES.)

If feasible, estrogens should be discontinued at least 4 to 6 weeks before surgery of the type associated with an increased risk of thromboembolism, or during periods of prolonged immobilization.

2. Malignant Neoplasms

a. Endometrial cancer

The use of unopposed estrogens in women with intact uteri has been associated with an increased risk of endometrial cancer. The reported endometrial cancer risk among unopposed estrogen users is about 2 to 12 times greater than in non-users, and appears dependent on duration of treatment and on estrogen dose. Most studies show no significant increased risk associated with use of estrogens for less than 1 year. The greatest risk appears associated with prolonged use, with increased risk of 15- to 24-fold for 5 to 10 years or more. This risk has been shown to persist for at least 8 to 15 years after estrogen therapy is discontinued.

Clinical surveillance of all women taking estrogen/progestin combinations is important. Adequate diagnostic measures, including endometrial sampling when indicated, should be undertaken to rule out malignancy in all cases of undiagnosed persistent or recurring abnormal vaginal bleeding. There is no evidence that the use of natural estrogens results in a different endometrial risk profile than synthetic estrogens of equivalent estrogen dose. Adding a progestin to estrogen therapy has been shown to reduce the risk of endometrial hyperplasia, which may be a precursor to endometrial cancer.

b. Breast Cancer

In some studies, the use of estrogens and progestins by postmenopausal women has been reported to increase the risk of breast cancer. The most important randomized clinical trial providing information about this issue is the Women's Health Initiative (WHI) (see CLINICAL STUDIES). The results from observational studies are generally consistent with those of the WHI clinical trial.

Observational studies have also reported an increased risk of breast cancer for estrogen-plus-progestin combination therapy, and a smaller increased risk for estrogen-alone therapy, after several years of use. For both findings, the excess risk increased with duration of use, and appeared to return to baseline over about five years after stopping treatment (only the observational studies have substantial data on risk after stopping). In these studies, the risk of breast cancer was greater, and became apparent earlier, with estrogen-plus-progestin combination therapy as compared to estrogen-alone therapy. However, these studies have not found significant variation in the risk of breast cancer among different estrogens or among different estrogen-plus-progestin combinations, doses, or routes of administration.

In the estrogen-alone substudy of WHI, after an average of 7.1 years of follow-up, CE (0.625 mg daily) was not associated with an increased risk of invasive breast cancer (RR 0.80, 95 % nCI 0.62-1.04).

In the estrogen-plus-progestin substudy, after a mean follow-up of 5.6 years, the WHI substudy reported an increased risk of breast cancer. In this substudy, prior use of estrogen-alone or estrogen/progestin combination hormone therapy was reported by 26% of the women. The relative risk of invasive breast cancer was 1.24 (95% nCI, 1.01-1.54), and the absolute risk was 41 versus 33 cases per 10,000 women-years, for estrogen-plus-progestin compared with placebo, respectively. Among women who reported prior use of hormone therapy, the relative risk of invasive breast cancer was 1.86, and the absolute risk was 46 versus 25 cases per 10,000 women-years, for estrogen-plus-progestin compared with placebo. Among women who reported no prior use of hormone therapy, the relative risk of invasive breast cancer was 1.09, and the absolute risk was 40 versus 36 cases per 10,000 women-years for estrogen-plus-progestin compared with placebo. In the WHI trial, invasive breast cancers were larger and diagnosed at a more advanced stage in the estrogen-plus-progestin group compared with the placebo group. Metastatic disease was rare with no apparent difference between the two groups. Other prognostic factors such as histologic subtype, grade and hormone receptor status did not differ between the groups.

The use of estrogen-alone and estrogen-plus-progestin has been reported to result in an increase in abnormal mammograms requiring further evaluation.

All women should receive yearly breast examinations by a healthcare provider and perform monthly breast self-examinations. In addition, mammography examinations should be scheduled based on patient age, risk factors, and prior mammogram results.

3. Dementia

In the estrogen-alone Women's Health Initiative Memory Study (WHIMS), a substudy of WHI, a population of 2,947 hysterectomized women aged 65 to 79 years was randomized to CE (0.625 mg daily) or placebo. In the estrogen-plus-progestin WHIMS, a population of 4,532 postmenopausal women aged 65 to 79 years was randomized to CE/MPA (0.625 mg/2.5 mg daily) or placebo.

In the estrogen-alone substudy, after an average follow-up of 5.2 years, 28 women in the estrogen-alone group and 19 women in the placebo group were diagnosed with probable dementia. The relative risk of probable dementia for CE alone versus placebo was 1.49 (95% CI, 0.83-2.66). The absolute risk of probable dementia for CE alone versus placebo was 37 versus 25 cases per 10,000 women-years.

In the estrogen-plus-progestin substudy, after an average follow-up of 4 years, 40 women in the estrogen-plus-progestin group and 21 women in the placebo group were diagnosed with probable dementia. The relative risk of probable dementia for estrogen-plus-progestin versus placebo was 2.05 (95% CI, 1.21-3.48). The absolute risk of probable dementia for CE/MPA versus placebo was 45 versus 22 cases per 10,000 women-years.

When data from the two populations were pooled as planned in the WHIMS protocol, the reported overall relative risk for probable dementia was 1.76 (95% CI 1.19-2.60). Since both substudies were conducted in women aged 65 to 79 years, it is unknown whether these findings apply to younger postmenopausal women. (see BOXED WARNINGS and PRECAUTIONS, and Geriatric Use.)

4. Gallbladder Disease

A two- to four-fold increase in the risk of gallbladder disease requiring surgery in postmenopausal women receiving estrogens has been reported.

5. Hypercalcemia

Estrogen administration may lead to severe hypercalcemia in patients with breast cancer and bone metastases. If hypercalcemia occurs, use of the drug should be stopped and appropriate measures taken to reduce the serum calcium level.

6. Visual Abnormalities

Retinal vascular thrombosis has been reported in patients receiving estrogens. Discontinue medication pending examination if there is sudden partial or complete loss of vision, or a sudden onset of proptosis, diplopia, or migraine. If examination reveals papilledema or retinal vascular lesions, estrogens should be permanently discontinued.

PRECAUTIONS

A. General

1. Addition of a progestin when a woman has not had a hysterectomy

Studies of the addition of a progestin for 10 or more days of a cycle of estrogen administration, or daily with estrogen in a continuous regimen, have reported a lowered incidence of endometrial hyperplasia than would be induced by estrogen treatment alone. Endometrial hyperplasia may be a precursor to endometrial cancer.

There are, however, possible risks that may be associated with the use of progestins with estrogens compared to estrogen-alone regimens. These include a possible increased risk of breast cancer, adverse effects on lipoprotein metabolism (e.g., lowering HDL, raising LDL), and impairment of glucose tolerance.

2. Elevated blood pressure

In a small number of case reports, substantial increases in blood pressure have been attributed to idiosyncratic reactions to estrogens. In a large, randomized, placebo-controlled clinical trial, a generalized effect of estrogens on blood pressure was not seen. Blood pressure should be monitored at regular intervals with estrogen use.

3. Hypertriglyceridemia

In patients with pre-existing hypertriglyceridemia, estrogen therapy may be associated with elevations of plasma triglycerides leading to pancreatitis and other complications.

4. Impaired liver function and past history of cholestatic jaundice

Estrogens may be poorly metabolized in patients with impaired liver function. For patients with a history of cholestatic jaundice associated with past estrogen use or with pregnancy, caution should be exercised, and in the case of recurrence, medication should be discontinued.

5. Hypothyroidism

Estrogen administration leads to increased thyroid-binding globulin (TBG) levels. Patients with normal thyroid function can compensate for the increased TBG by making more thyroid hormone, thus maintaining free T4 and T3 serum concentrations in the normal range. Patients dependent on thyroid hormone replacement therapy who are also receiving estrogens may require increased doses of their thyroid replacement therapy. These patients should have their thyroid function monitored to maintain their free thyroid hormone levels in an acceptable range.

6. Fluid retention

Estrogens may cause some degree of fluid retention. Because of this, patients who have conditions that might be influenced by this factor, such as a cardiac or renal dysfunction, warrant careful observation when estrogens are prescribed.

7. Hypocalcemia

Estrogens should be used with caution in individuals with severe hypocalcemia.

8. Ovarian cancer

The estrogen-plus-progestin substudy of the WHI reported that after an average follow-up of 5.6 years, the relative risk for ovarian cancer for estrogen-plus-progestin versus placebo was 1.58 (95% nCI, 0.77-3.24), but was not statistically significant. The absolute risk for estrogen-plus-progestin versus placebo was 4.2 versus 2.7 cases per 10,000 women-years. In some epidemiologic studies, the use of estrogen only products in particular for 10 or more years, has been associated with an increased risk of ovarian cancer. Other epidemiologic studies have not found these associations.

9. Exacerbation of endometriosis

Endometriosis may be exacerbated with administration of estrogens. Malignant transformation of residual endometrial implants have been reported in women treated post-hysterectomy with estrogen-alone therapy. For patients known to have residual endometriosis post-hysterectomy, the addition of progestin should be considered.

10. Exacerbation of other conditions

Estrogens may cause an exacerbation of asthma, diabetes mellitus, epilepsy, migraine or porphyria, systemic lupus erythematosus, and hepatic hemangiomas and should be used with caution in women with these conditions.

11. Photosensitivity/Photoallergy

The effects of direct sun exposure to Divigel® application sites have not been evaluated in clinical trials. Nonclinical studies in guinea pigs showed no phototoxicity or photosensitivity. In addition, Divigel® has been shown to absorb light primarily at wavelengths below 290 nm. Therefore, Divigel® is not considered to have photosensitizing potential.

12. Sunscreen application

Studies conducted using other approved topical estrogen gel products have shown that sunscreens have the potential for changing the systemic exposure of topically applied estrogen gels. The effect of concomitant application of sunscreen and Divigel® to the same application site has not been clinically evaluated.

13. Miscellaneous

Alcohol based gels are flammable. Avoid fire, flame, or smoking until the gel has dried.

Occlusion of the area where the topical drug product is applied with clothing or other barriers is not recommended until the gel is completely dried.

14. Potential for Estradiol Transfer and Effects of Washing

There is a potential for drug transfer from one individual to the other following physical contact of Divigel® application sites. In a study to evaluate transferability to males from their female contacts, there was some elevation of estradiol levels over baseline in the male subjects, however, the degree of transferability in this study was inconclusive. Patients are advised to avoid skin contact with other subjects until the gel is completely dried. The site of application should be covered (clothed) after drying.

Washing the application site with soap and water 1 hour after application resulted in a 30 to 38% decrease in the mean total 24-hour exposure to estradiol. Therefore, patients should refrain from washing the application site for at least one hour after application.

B. Information for Patients

Physicians and pharmacists are advised to discuss the PATIENT INFORMATION leaflet with patients for whom they prescribe or dispense Divigel®.

C. Laboratory Tests

Estrogen administration should be initiated at the lowest dose approved for the treatment of moderate-to-severe vasomotor symptoms associated with menopause and then guided by clinical response rather than by serum hormone levels (e.g., estradiol, FSH).

D. Drug and Laboratory Test Interactions

1. Accelerated prothrombin time, partial thromboplastin time, and platelet aggregation time; increased platelet count; increased factors II, VII antigen, VIII antigen, VIII coagulant activity, IX, X, XII, VII-X complex, II-VII-X complex, and beta-thromboglobulin; decreased levels of anti-factor Xa and antithrombin III, decreased antithrombin III activity; increased levels of fibrinogen and fibrinogen activity; increased plasminogen antigen and activity.
2. Increased thyroid binding globulin (TBG) levels leading to increased circulating total thyroid hormone levels, as measured by protein-bound iodine (PBI), T4 levels (by column or by radioimmunoassay) or T3 levels by radioimmunoassay. T3 resin uptake is decreased, reflecting the elevated TBG. Free T4 and free T3 concentrations are unaltered. Patients on thyroid replacement therapy may require higher doses of thyroid hormone.
3. Other binding proteins may be elevated in serum (i.e., corticosteroid binding globulin (CBG), sex hormone binding globulin (SHBG) leading to increased total circulating corticosteroids and sex steroids, respectively. Free hormone concentrations may be decreased. Other plasma proteins may be increased (angiotensinogen/renin substrate, alpha-l-antitrypsin, ceruloplasmin).
4. Increased plasma HDL and HDL2 cholesterol subfraction concentrations, reduced LDL cholesterol concentration, increased triglyceride levels.
5. Impaired glucose tolerance.
6. Reduced response to metyrapone test.

E. Carcinogenesis, Mutagenesis, Impairment of Fertility

See BOXED WARNINGS, WARNINGS and PRECAUTIONS.

Long-term continuous administration of natural and synthetic estrogens in certain animal species increases the frequency of carcinomas of the breast, uterus, cervix, vagina, testis and liver.

F. Pregnancy

Estrogen products, including Divigel®, should not be used in pregnancy. (See CONTRAINDICATIONS.)

G. Nursing Mothers

Estrogen administration to nursing mothers has been shown to decrease the quantity and quality of the milk. Detectable amounts of estrogens have been identified in the milk of mothers receiving estrogen therapy. Caution should be exercised when estrogen products, including Divigel®, are administered to a nursing woman.

H. Pediatric Use

Safety and efficacy of Divigel® in pediatric patients has not been established.

I. Geriatric Use

There have not been sufficient numbers of geriatric patients involved in studies utilizing Divigel® to determine whether those over 65 years of age differ from younger subjects in their response to Divigel®.

Of the total number of subjects in the estrogen-alone substudy of the Women's Health Initiative (WHI), 46% (n=4,943) were 65 years and older, while 7.1% (n=767) were 75 years and older. There was a higher relative risk (CE versus placebo) of stroke in women less than 75 years of age compared to women 75 years and older.

In the estrogen-alone substudy of the Women's Health Initiative Memory Study (WHIMS), a substudy of WHI, a population of 2,947 hysterectomized women, aged 65 to 79 years, was randomized to CE (0.625 mg per day) or placebo. After an average follow-up of 5.2 years, the relative risk (CE versus placebo) of probable dementia was 1.49 (95% CI, 0.83-2.66). The absolute risk of developing probable dementia with estrogen alone was 37 vs. 25 cases per 10,000 women-years with placebo.

Of the total number of subjects in the estrogen-plus-progestin substudy of the WHI, 44% (n=7,320) were 65 years and older, while 6.6% (n=1,095) were 75 years and older. There was a higher relative risk (CE/MPA versus placebo) of stroke and invasive breast cancer in women 75 and older compared to women less than 75 years of age. In women greater than 75, the increased risk of non-fatal stroke and invasive breast cancer observed in the estrogen-plus-progestin combination group compared to the placebo group was 75 vs. 24 per 10,000 women-years and 52 vs. 12 per 10,000 women years, respectively.

In the estrogen-plus-progestin substudy of WHIMS, a population of 4,532 postmenopausal women, aged 65 to 79 years, was randomized to CE/MPA (CE 0.625 mg/2.5 mg daily) or placebo. In the estrogen-plus-progestin group, after an average follow-up of 4 years, the relative risk (CE/MPA versus placebo) of probable dementia was 2.05 (95% CI, 1.21-3.48). The absolute risk of developing probable dementia with CE/MPA was 45 vs. 22 cases per 10,000 women-years with placebo.

Seventy-nine percent of the cases of probable dementia occurred in women that were older than 70 for the CE group, and 82 percent of the cases of probable dementia occurred in women who were older than 70 in the CE/MPA group. The most common classification of probable dementia in both the treatment groups and placebo groups was Alzheimer's disease.

When data from the two populations were pooled as planned in the WHIMS protocol, the reported overall risk of probable dementia was 1.76 (95% CI, 1.19-2.60). Since both substudies were conducted in women aged 65 to 79 years, it is unknown whether these findings apply to younger postmenopausal women. (See BOXED WARNINGS, and WARNINGS, Dementia.)

ADVERSE REACTIONS

See BOXED WARNINGS, WARNINGS and PRECAUTIONS.

Because clinical trials are conducted under widely varying conditions, adverse reaction rates observed in the clinical trials of a drug cannot be directly compared to rates in the clinical trials of another drug and may not reflect the rates observed in practice. The adverse reaction information from clinical trials does, however, provide a basis for identifying the adverse events that appear to be related to drug use and for approximating rates.

Divigel® was studied at doses of 0.25, 0.5 and 1.0 g/day in a 12-week, double-blind, placebo-controlled study that included a total of 495 postmenopausal women (86.5% Caucasian). The adverse events that occurred at a rate greater than 5% in any of the treatment groups are summarized in Table 5.

Table 5: Number (%) of Subjects with Common Adverse Events* in a 12-Week Placebo- Controlled Study of Divigel®
 | Divigel® |  |  | Placebo
 | 0.25 g/day | 0.5 g/day | 1.0 g/day
SYSTEM ORGAN CLASS | N=122 | N=123 | N=125 | N=125
Preferred Term | n (%) | n (%) | n (%) | n (%)
INFECTIONS & INFESTATIONS
Nasopharyngitis | 7 (5.7) | 5 (4.1) | 6 (4.8) | 5 (4.0)
Upper Respiratory Tract Infection | 7 (5.7) | 3 (2.4) | 2 (1.6) | 2 (1.6)
Vaginal mycosis | 1 (0.8) | 3 (2.4) | 8 (6.4) | 4(3.2)
REPRODUCTIVE SYSTEM & BREAST DISORDERS
Breast Tenderness | 3 (2.5) | 7 (5.7) | 11 (8.8) | 2 (1.6)
Metrorrhagia | 5 (4.1) | 7 (5.7) | 12 (9.6) | 2 (1.6)
* Adverse events reported by ≥5% of patients in any treatment group.

In a 12-week placebo-controlled study of Divigel®, application site reactions were seen in <1% of subjects.

The following additional adverse reactions have been reported with estrogen and/or progestin therapy.

1. Genitourinary system: Changes in vaginal bleeding pattern and abnormal withdrawal bleeding or flow; breakthrough bleeding; spotting; dysmenorrhea; increase in size of uterine leiomyomata; vaginitis, including vaginal candidiasis; change in amount of cervical secretion; changes in cervical ectropion; ovarian cancer; endometrial hyperplasia; endometrial cancer; vaginal discharge.
2. Breasts: Tenderness; enlargement, pain, nipple discharge, galactorrhea, fibrocystic breast changes; breast cancer; nipple pain.
3. Cardiovascular: Deep and superficial venous thrombosis, pulmonary embolism; thrombophlebitis; myocardial infarction; stroke; increase in blood pressure.
4. Gastrointestinal: Nausea; vomiting; abdominal cramps; bloating; cholestatic jaundice; increased incidence of gallbladder disease; pancreatitis; enlargement of hepatic hemangiomas; abdominal pain.
5. Skin: Chloasma or melasma, which may persist when drug is discontinued; erythema multiforme; erythema nodosum; hemorrhagic eruption; loss of scalp hair; hirsutism; pruritus; rash.
6. Eyes: Retinal vascular thrombosis, intolerance to contact lenses.
7. Central Nervous System: Headache; migraine; dizziness; mental depression; chorea; nervousness; mood disturbances; irritability; exacerbation of epilepsy; dementia.
8. Miscellaneous: Increase or decrease in weight; reduced carbohydrate tolerance; aggravation of porphyria; edema; arthralgias; leg cramps; changes in libido; urticaria; angioedema; anaphylactoid/anaphylactic reactions; hypocalcemia; exacerbation of asthma; increased triglycerides; muscle cramps.

OVERDOSAGE

Serious ill effects have not been reported following acute ingestion of large doses of estrogen-containing drug products by young children. Overdosage of estrogen may cause nausea and vomiting, and withdrawal bleeding may occur in females.

DOSAGE AND ADMINISTRATION

When estrogen is prescribed for a postmenopausal woman with a uterus, a progestin should also be initiated to reduce the risk of endometrial cancer. A woman without a uterus does not need progestin. Use of estrogen, alone or in combination with a progestin, should be with the lowest effective dose and for the shortest duration consistent with treatment goals and risks for the individual woman. Patients should be re-evaluated periodically as clinically appropriate (e.g., 3-month to 6-month intervals) to determine if treatment is still necessary (see BOXED WARNINGS and WARNINGS). For women who have a uterus, adequate diagnostic measures, such as endometrial sampling, when indicated, should be undertaken to rule out malignancy in cases of undiagnosed persistent or recurring abnormal vaginal bleeding.

Divigel® (estradiol gel) 0.1%, at doses of 0.25, 0.5, and 1.0 g/day, is indicated for topical use in the treatment of moderate to severe vasomotor symptoms associated with menopause. Each gram of Divigel® contains 1 mg of estradiol.

Patients should be treated with the lowest effective dose of Divigel®. Generally, women should be started at 0.25 gram Divigel® daily. Subsequent dosage adjustments may be made based upon the individual patient response. This dose should be periodically reassessed by the healthcare provider.

Divigel® should be applied once daily on the skin of either the right or left upper thigh. The application surface area should be about 5 by 7 inches (approximately the size of two palm prints). The entire contents of a unit dose packet should be applied each day. To avoid potential skin irritation, Divigel® should be applied to the right or left upper thigh on alternating days. Divigel® should not be applied on the face, breasts, or irritated skin or in or around the vagina. After application, the gel should be allowed to dry before dressing. The application site should not be washed within 1 hour after applying Divigel®. Contact of the gel with eyes should be avoided. Hands should be washed after application.

HOW SUPPLIED

Divigel® (estradiol gel) 0.1% is a clear, colorless, smooth, opalescent gel supplied in single-dose foil packets of 1.0 g, corresponding to 1.0 mg estradiol, respectively.

NDC 54868-6056-0, carton of 30 packets, 1.0 mg estradiol per single-dose foil packet

Keep out of the reach of children.

Store at 20 to 25°C (68 to 77°F). Excursions permitted to 15 to 30°C (59 to 86°F). [See USP Controlled Room Temperature.]

Manufactured by
Orion Corporation Orion Pharma
Tengströminkatu 8
FI-20360 Turku
Finland

Distributed by
Upsher-Smith Laboratories, Inc.
Minneapolis, MN 55447

1-800-654-2299

Product of Finland

Revised June 2007

Relabeling of "Additional Barcode" by
Physicians Total Care, Inc.
Tulsa, OK 74146

PATIENT INFORMATION

(Updated June 2007)

Divigel®

(estradiol gel) 0.1%

Read this PATIENT INFORMATION leaflet before you start using Divigel® and read what you get each time you refill your Divigel® prescription. There may be new information. This information does not take the place of talking to your healthcare provider about your medical condition or your treatment.

WHAT IS THE MOST IMPORTANT INFORMATION I SHOULD KNOW
ABOUT Divigel® (AN ESTROGEN HORMONE)?

- Estrogens increase the chance of getting cancer of the uterus. Report any unusual vaginal bleeding right away while you are taking estrogens. Vaginal bleeding after menopause may be a warning sign of cancer of the uterus (womb). Your healthcare provider should check any unusual vaginal bleeding to find out the cause.
- Do not use estrogens, with or without progestins, to prevent heart disease, heart attacks, or strokes. Using estrogens, with or without progestins, may increase your chance of getting heart attacks, strokes, breast cancer, and blood clots.
- Do not use estrogens, with or without progestins, to prevent dementia. Using estrogens, with or without progestins, may increase your risk of dementia.
  You and your healthcare provider should talk regularly about whether you still need treatment with Divigel®.

What is Divigel®?

Divigel® is a medicine that contains an estrogen hormone (estradiol). Divigel® is a clear, colorless, smooth gel that is odorless when dry.

What is Divigel® used for?

Divigel® is used after menopause to:

- Reduce moderate to severe hot flashes

Estrogens are hormones made by a woman's ovaries. The ovaries normally stop making estrogens when a woman is between 45 to 55 years old. This drop in body estrogen levels causes the “change of life” or menopause (the end of monthly menstrual periods). Sometimes, both ovaries are removed during an operation before natural menopause takes place. The sudden drop in estrogen levels causes “surgical menopause.”

When the estrogen levels begin dropping, some women develop very uncomfortable symptoms, such as feelings of warmth in the face, neck, and chest, or sudden strong feelings of heat and sweating (“hot flashes” or “hot flushes”). In some women, the symptoms are mild, and they will not need estrogens. In other women, symptoms can be more severe. You and your healthcare provider should talk regularly about whether you still need treatment with Divigel®.

Who should not use Divigel®?

Do not start using Divigel® if you:

- Have unusual vaginal bleeding
- Currently have or have had certain cancers

Estrogens may increase the chances of getting certain types of cancers, including cancer of the breast or uterus. If you have or have had cancer, talk with your healthcare provider about whether you should use Divigel®.

- Had a stroke or heart attack in the past year
- Currently have or have had blood clots
- Currently have or have had liver problems
- Are allergic to Divigel® or any of its ingredients

See the next section of this leaflet for a list of ingredients in Divigel®.

- Think you may be pregnant

TELL YOUR HEALTHCARE PROVIDER:

- If you are breastfeeding

The hormone in Divigel® can pass into your milk.

- About all of your medical problems

Your healthcare provider may need to check you more carefully if you have certain conditions, such as asthma (wheezing); epilepsy (seizures); migraine; endometriosis; lupus; problems with your heart, liver, thyroid, or kidneys; or have high calcium levels in your blood.

- About all the medicines you take

This includes prescription and nonprescription medicines, vitamins, and herbal supplements. Some medicines may affect how Divigel® works. Divigel® may also affect how your other medicines work.

- If you are going to have surgery or will be on bedrest

You may need to stop using Divigel®.

What are the ingredients in Divigel®?

The active ingredient in Divigel® is estradiol.

The inactive ingredients are carbomer, ethanol, propylene glycol, purified water, and triethanolamine.

How should I use Divigel®?

1. Divigel® should be used once daily.
2. Start at the lowest dose and talk to your healthcare provider about how well that dose is working for you.
3. Divigel® should be used at the lowest dose possible for your treatment and only as long as needed.

You and your healthcare provider should talk regularly (for example, every 3 to 6 months) about the dose you are taking and whether you still need treatment with Divigel®.

Important things to remember when using Divigel®

- Wash your hands with soap and water after applying the gel to reduce the chance that the medicine will be spread from your hands to other people.
- Allow the gel to dry before dressing. Try to keep the area dry for as long as possible.
- Do not allow others to come in contact with the area of skin where you applied the gel for at least one hour after you apply Divigel®.
- You should not allow others to apply the gel for you. However, if this is necessary, the individual should wear a disposable plastic glove to avoid direct contact with Divigel®
- Do not apply Divigel® to your face, breast, or irritated skin.
- Never apply Divigel® in or around the vagina.
- Divigel® contains alcohol. Alcohol based gels are flammable. Avoid fire, flame or smoking until the gel has dried.

What should I do if I miss a dose?

If you miss a dose, do not double the dose on the next day to catch up. If your next dose is less than 12 hours away, it is best just to wait and apply your normal dose the next day. If it is more than 12 hours until the next dose, apply the dose you missed and resume your normal dosing the next day. Do not apply Divigel® more than once each day. If you accidentally spill some of the contents of a Divigel® packet, do not open a new packet. Wait and apply your normal dose the next day.

What should I do if someone else is exposed to Divigel®?

Once you have applied Divigel®, it has dried, and you have washed your hands, there is little risk of transfer to another person. If someone else is exposed to Divigel® by direct contact with the wet gel, that person should wash the area of contact with soap and water as soon as possible. This is especially important for men and children. The longer the gel is in contact with the skin before washing, the chance is greater that the other person will absorb some of the estrogen hormone.

What should I do if I get Divigel® in my eyes?

If you get Divigel® in your eyes, flush your eyes right away with lukewarm tap water. If you have concerns, contact your healthcare provider.

What are the possible side effects of estrogens?

Less common but serious side effects include:

- Breast cancer
- Cancer of the uterus
- Stroke
- Heart attack
- Blood clots
- Dementia
- Gallbladder disease
- Ovarian cancer

Some of the warning signs of serious side effects include:

- Breast lumps
- Unusual vaginal bleeding
- Dizziness and faintness
- Changes in speech
- Severe headaches
- Chest pain
- Shortness of breath
- Pains in your legs
- Changes in vision
- Vomiting

Call your healthcare provider right away if you get any of these warning signs, or any other unusual symptom that concerns you.

Common side effects include:

- Headache
- Breast pain
- Irregular vaginal bleeding or spotting
- Stomach/abdominal cramps, bloating
- Nausea and Vomiting
- Hair loss

Other side effects include:

- High blood pressure
- Liver problems
- High blood sugar
- Fluid retention
- Enlargement of benign tumors of the uterus (“fibroids”)
- Vaginal yeast infection

These are not all the possible side effects of Divigel®. For more information, ask your healthcare provider or pharmacist.

What can I do to lower my chances of a serious side effect with Divigel®?

Talk with your healthcare provider regularly about whether you should continue taking Divigel®. If you have a uterus, talk to your healthcare provider about whether the addition of a progestin is right for you. In general, the addition of a progestin is recommended for women with a uterus to reduce the chance of getting cancer of the uterus. See your healthcare provider right away if you get vaginal bleeding while taking Divigel®. Have a breast exam and mammogram (breast X-ray) every year unless your healthcare provider tells you otherwise. If members of your family have had breast cancer or if you have ever had breast lumps or an abnormal mammogram, you may need to have breast exams more often. If you have high blood pressure, high cholesterol (fat in the blood), diabetes, are overweight, or if you use tobacco, you may have higher chances of getting heart disease. Ask your healthcare provider for ways to lower your chances of getting heart disease.

Have an annual gynecological exam.

General information about safe and effective use of Divigel®

Medicines are sometimes prescribed for conditions that are not mentioned in patient information leaflets. Do not use Divigel® for conditions for which it was not prescribed. Do not give Divigel® to other people, even if they have the same symptoms you have. It may harm them.

Keep Divigel® out of the reach of children.

This leaflet provides a summary of the most important information about Divigel®. If you would like more information, talk with your healthcare provider or pharmacist. You can ask for information about Divigel® that is written for health professionals. You can get more information by calling the toll free number 1-800-654-2299.

How should Divigel® be applied?

- Divigel® should be applied once a day, around the same time each day.
- Apply Divigel® to clean, dry, and unbroken (without cuts or scrapes) skin. If you take a bath or shower, be sure to apply your Divigel® after your skin is dry. The application site should be completely dry before dressing or swimming.
- Apply Divigel® to either your left or right upper thigh. Change between your left and right upper thigh each day to help prevent skin irritation.

TO APPLY:

1. Wash and dry your hands thoroughly.
2. Sit in a comfortable position.
3. Cut or tear the Divigel® packet as shown in Diagram 1.
  Diagram 1.
4. Using your thumb and index finger, squeeze the entire contents of the packet onto the skin of the upper thigh as shown in Diagram 2.
  Diagram 2.
5. Gently spread the gel in a thin layer on your upper thigh over an area of about 5 by 7 inches, or two palm prints as shown in Diagram 3. It is not necessary to massage or rub in Divigel®.
  Diagram 3.
6. Allow the gel to dry completely before dressing.
7. Dispose of the empty Divigel® packet in the trash.
8. Wash your hands with soap and water immediately after applying Divigel® to remove any remaining gel and reduce the chance of transferring Divigel® to other people.

HOW IS Divigel® SUPPLIED?

Divigel® is supplied in individual foil packets, each one containing a single day's dose.

Store Divigel® packets at 20 to 25°C (68 to 77°F). Excursions permitted to 15 to 30°C (59 to 86°F). [See USP Controlled Room Temperature.]

Manufactured by
Orion Corporation Orion Pharma
Tengströminkatu 8
FI-20360 Turku
Finland

Distributed by
Upsher-Smith Laboratories, Inc.
Minneapolis, MN 55447
1-800-654-2299
Product of Finland

PRINCIPAL DISPLAY PANEL - 1mg/30-packet carton

Divigel®
(estradiol gel) 0.1%
1 mg

30 packets
1 g gel provides 1 mg estradiol/packet
Rx only